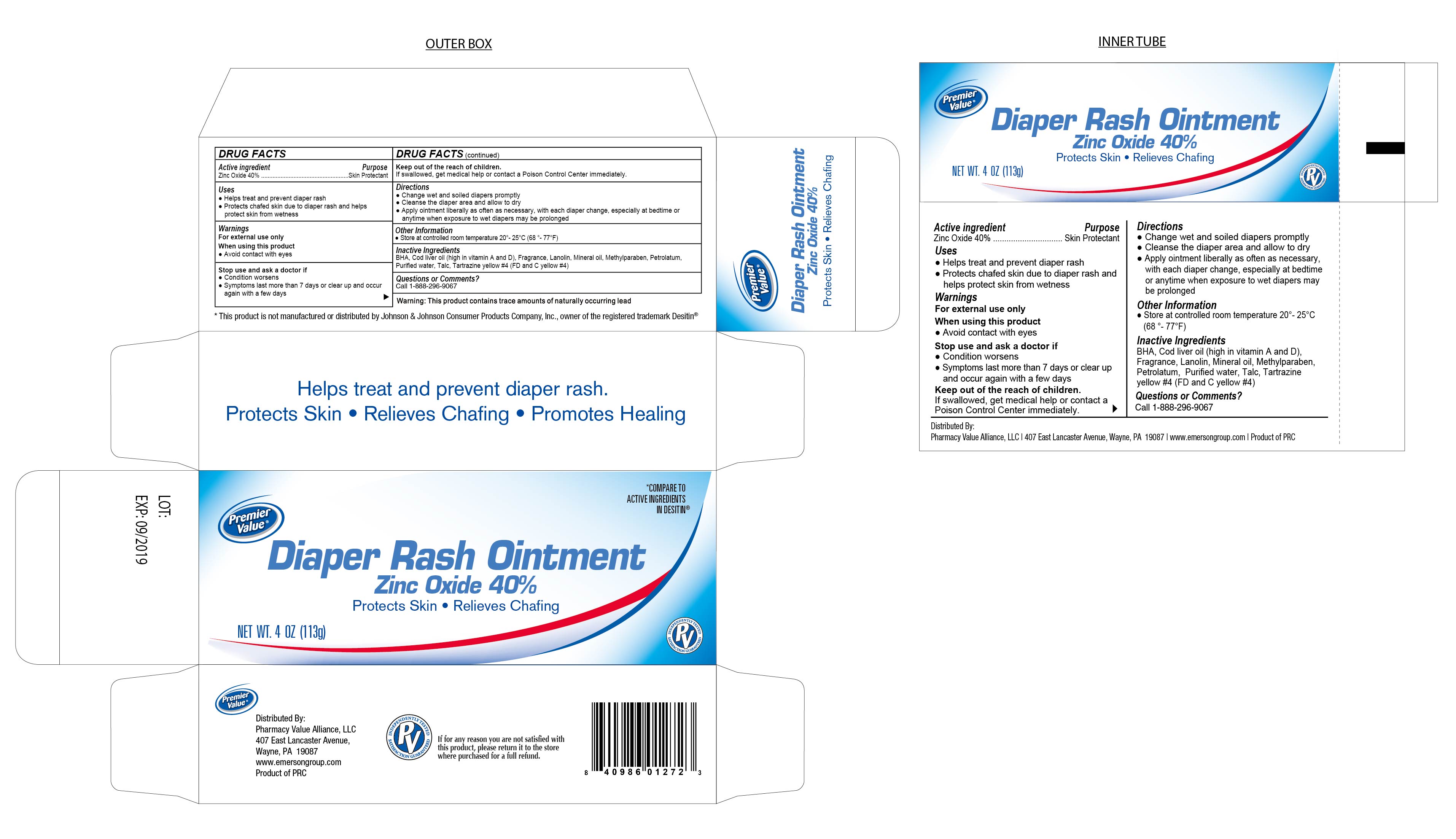 DRUG LABEL: DiaperRashOintment
NDC: 68016-128 | Form: OINTMENT
Manufacturer: Pharmacy Value Alliance, LLC
Category: otc | Type: HUMAN OTC DRUG LABEL
Date: 20241220

ACTIVE INGREDIENTS: ZINC OXIDE 40 g/100 g
INACTIVE INGREDIENTS: POLYSORBATE 80; ALPHA-TOCOPHEROL ACETATE; GLYCERYL MONOSTEARATE; PROPYLPARABEN; METHYLPARABEN; ALOE VERA LEAF; PETROLATUM; YELLOW WAX; STEARIC ACID; MINERAL OIL; WATER

Diaper Rash Ointment

Active Ingredient

Zinc Oxide 40%

Purpose

Skin Protectant

Uses

- Helps treat and prevent diaper rash
- Protects chafed skin due to diaper rash and helps protect skin from wetness

Keep out of the reach of children.

If swallowed, get medical help or contact a Poison Control Center immediately.

Warnings

For External Use Only

When using this product

- Avoid contact with eyes

Directions

- Change wet and soiled diapers promptly
- Cleanse the diaper area and allow to dry
- Apply ointment liberally as often as necessary, with each diaper change, especially at bedtime or anytime when exposure to wet diapers may be prolonged.

Stop use and ask a doctor if

- Condition worsens
- Symptoms last more than 7 days or clear up and occur again with a few days

Other Information:

- Store at controlled room temperature 20° - 25°C (68° - 77°F)

Inactive Ingredients

BHA, Cod liver oil (high in vitamin A and D), Frangrance, Lanolin, Mineral Oil, Methylparaben, Petrolatum, Purified water, Talc, Tartrazine yellow #4 (FD and C yellow #4)

Helps treat and prevent diaper rash. Protects skin. Relieves Chafing. Promotes Healing

Distributed by:

Pharmacy Value Alliance, LLC.

407 East Lancaster Avenue, Wayne, PA. 19087 USA

www.emersongroup.com